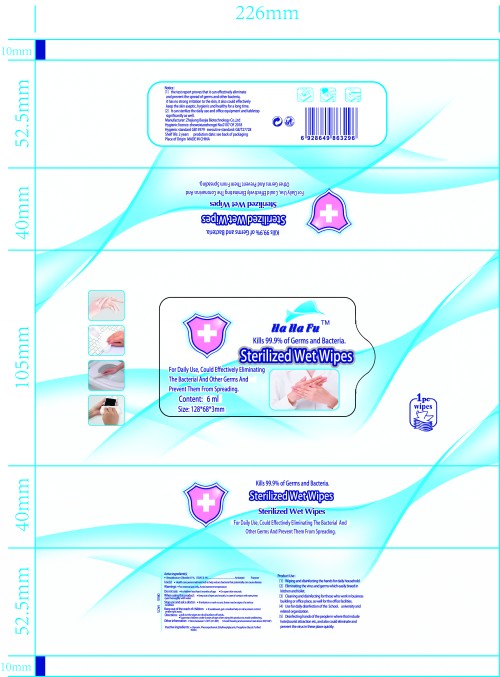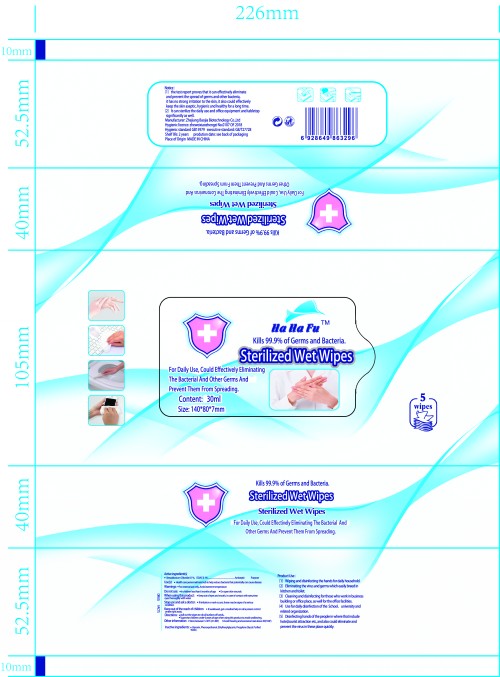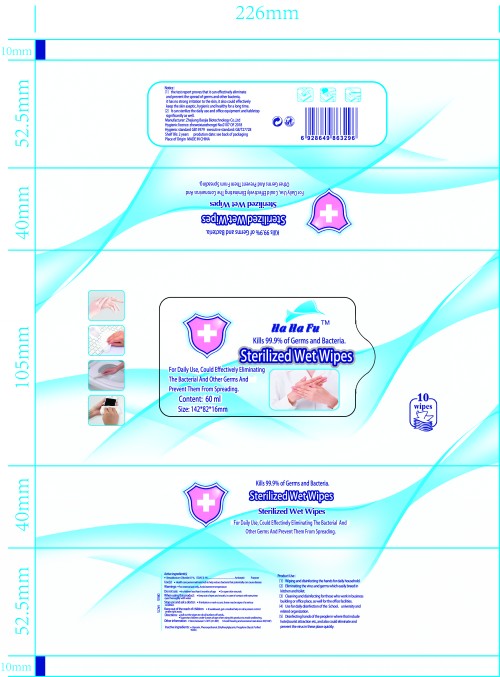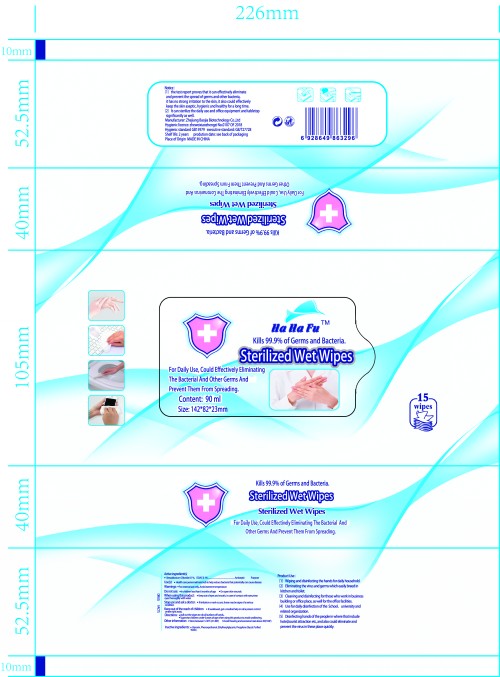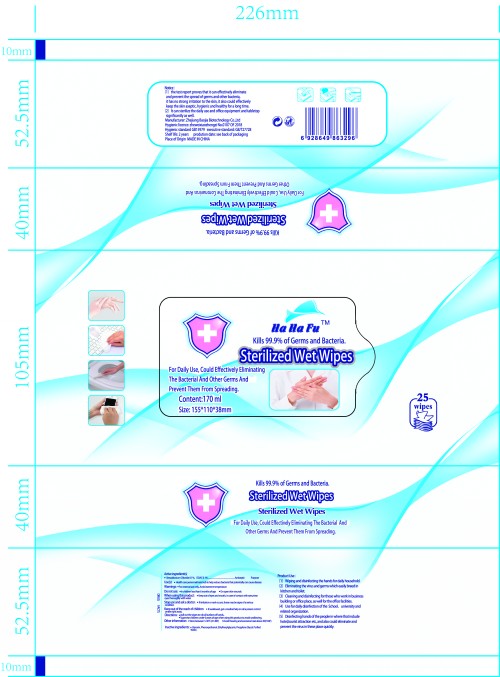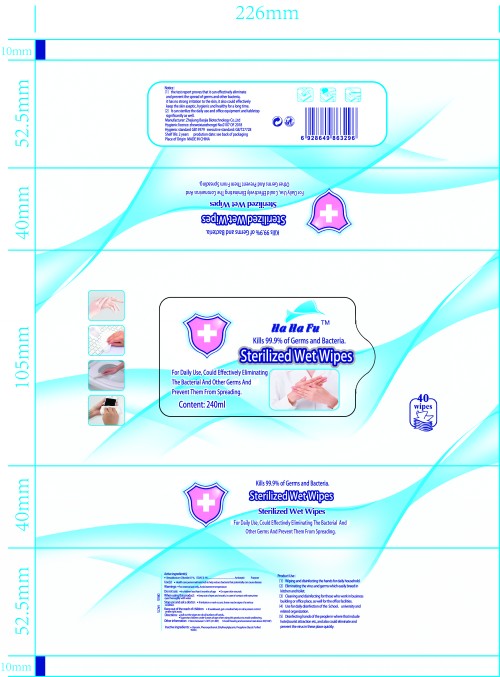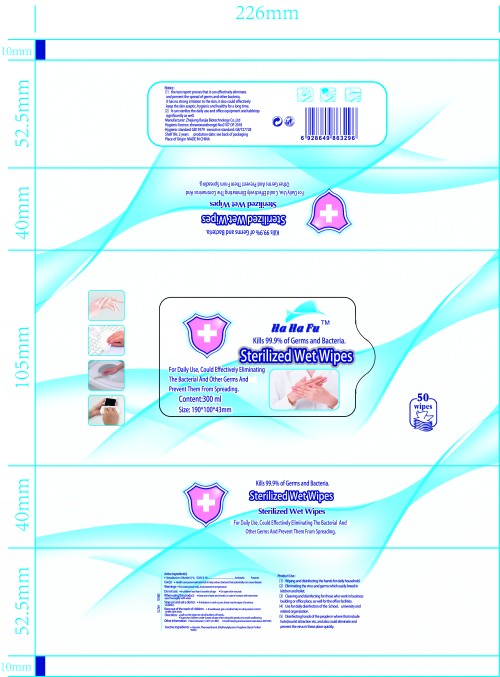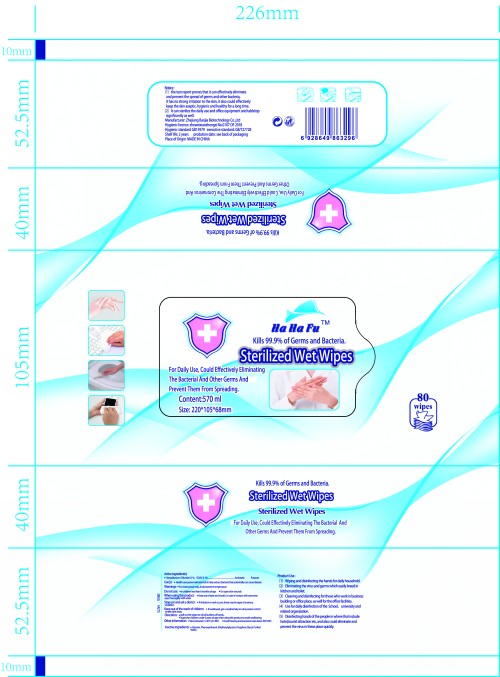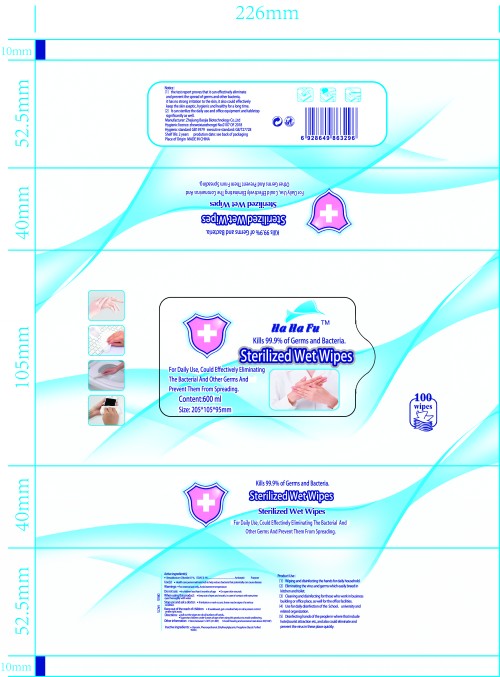 DRUG LABEL: Sterilized Wet Wipes
NDC: 78447-002 | Form: CLOTH
Manufacturer: ZHEJIANG BAOJIA BIOTECHNOLOGY CO., LTD.
Category: otc | Type: HUMAN OTC DRUG LABEL
Date: 20200612

ACTIVE INGREDIENTS: DIDECYLDIMONIUM CHLORIDE 0.1 g/100 mL; BENZALKONIUM CHLORIDE 0.1 g/100 mL
INACTIVE INGREDIENTS: ETHYLHEXYLGLYCERIN; PROPYLENE GLYCOL; GLYCERIN; PHENOXYETHANOL; WATER

Sterilized Wet Wipes

Active ingredient(s)

Benzalkonium Chloride 0.1%,DDAC 0.1%

Purpose

Antiseptic

Use(s)

Health care personnel hand rub to help reduce bacteria that potentially can cause diseaze.

Warnings

For extemal use only, Avoid extreme temperature

Do not use

In children less than 6 months of age

On open skin wounds

When using this product

Keep out of eyes and mouth, in case of contact with eyes,rinse eyes thoroughly with water.

Stop use and ask a doctor

lf iirritation or rash occurs, these may be signs of a serious condition.

Keep out of the reach of children

if swallowed,get a medical help or call a poison control center right away.

Directions

pull out the wipes to rub all surfaces of hands,.

Supervise children under 6 years of age when using this product to avoid swallowing.

Other information

Store between 5-30℃(41-86F)

Avoid freezing and excessive heat above 40(104F)

Inactive ingredients

Glycerin, Phenoxyethanol Ethylhexylglycerin, Propylene Glycol,Purfied Water.